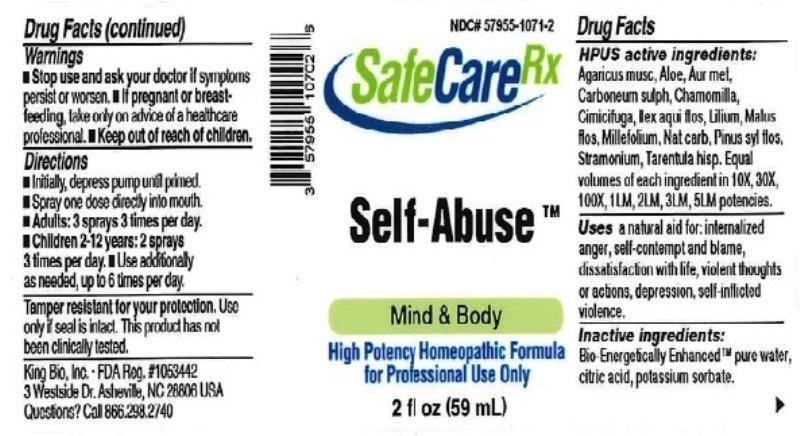 DRUG LABEL: Self-Abuse
NDC: 57955-1071 | Form: LIQUID
Manufacturer: King Bio Inc.
Category: homeopathic | Type: HUMAN OTC DRUG LABEL
Date: 20161115

ACTIVE INGREDIENTS: AMANITA MUSCARIA FRUITING BODY 10 [hp_X]/59 mL; ALOE 10 [hp_X]/59 mL; GOLD 10 [hp_X]/59 mL; CARBON DISULFIDE 10 [hp_X]/59 mL; MATRICARIA RECUTITA 10 [hp_X]/59 mL; BLACK COHOSH 10 [hp_X]/59 mL; ILEX AQUIFOLIUM FLOWERING TOP 10 [hp_X]/59 mL; LILIUM LANCIFOLIUM WHOLE FLOWERING 10 [hp_X]/59 mL; MALUS DOMESTICA FLOWER 10 [hp_X]/59 mL; ACHILLEA MILLEFOLIUM 10 [hp_X]/59 mL; SODIUM CARBONATE 10 [hp_X]/59 mL; PINUS SYLVESTRIS FLOWERING TOP 10 [hp_X]/59 mL; DATURA STRAMONIUM 10 [hp_X]/59 mL; LYCOSA TARANTULA 10 [hp_X]/59 mL
INACTIVE INGREDIENTS: WATER; ANHYDROUS CITRIC ACID; POTASSIUM SORBATE

Self-Abuse

ACTIVE INGREDIENT

Drug Facts__________________________________________________________________________________________________________

HPUS active ingredients: Agaricus muscarius, Aloe, Aurum metallicum, Carboneum sulphuratum, Chamomilla, Cimicifuga racemosa, Ilex aquifolium, flos, Lilium tigrinum, Malus pumila, flos, Millefolium, Natrum carbonicum, Pinus sylvestris, flos, Stramonium, Tarentula hispanica. Equal volumes of each ingredient in 10X, 30X, 100X, 1LM, 2LM, 3LM, 5LM potencies.

INDICATIONS AND USAGE

Uses a natural aid for: internalized anger, self-contempt and blame, dissatisfaction with life, violent thoughts or actions, depression, self-inflicted violence.

Inactive Ingredients:

Bio-Energetically Enhanced™ pure water, citric acid and potassium sorbate.

Warnings

- Stop use and ask your doctor if symptoms persist or worsen.
- If pregnant or breast-feeding, take only on advice of a healthcare professional.

- Keep out of reach of children.

Directions

- Initially, depress pump until primed.
- Spray one dose directly into mouth.
- Adults: 3 sprays 3 times per day
- Children 2-12 years: 2 sprays 3 times per day.
- Use additionally as needed, up to 6 times per day.

OTHER SAFETY INFORMATION

Tamper resistant for your protection. Use only if safety seal is intact. This product has not been clinically tested.

PURPOSE

Uses a natural aid for:

- internalized anger
- self-contempt and blame
- dissatisfaction with life
- violent thoughts or actions
- depression
- self-inflicted violence